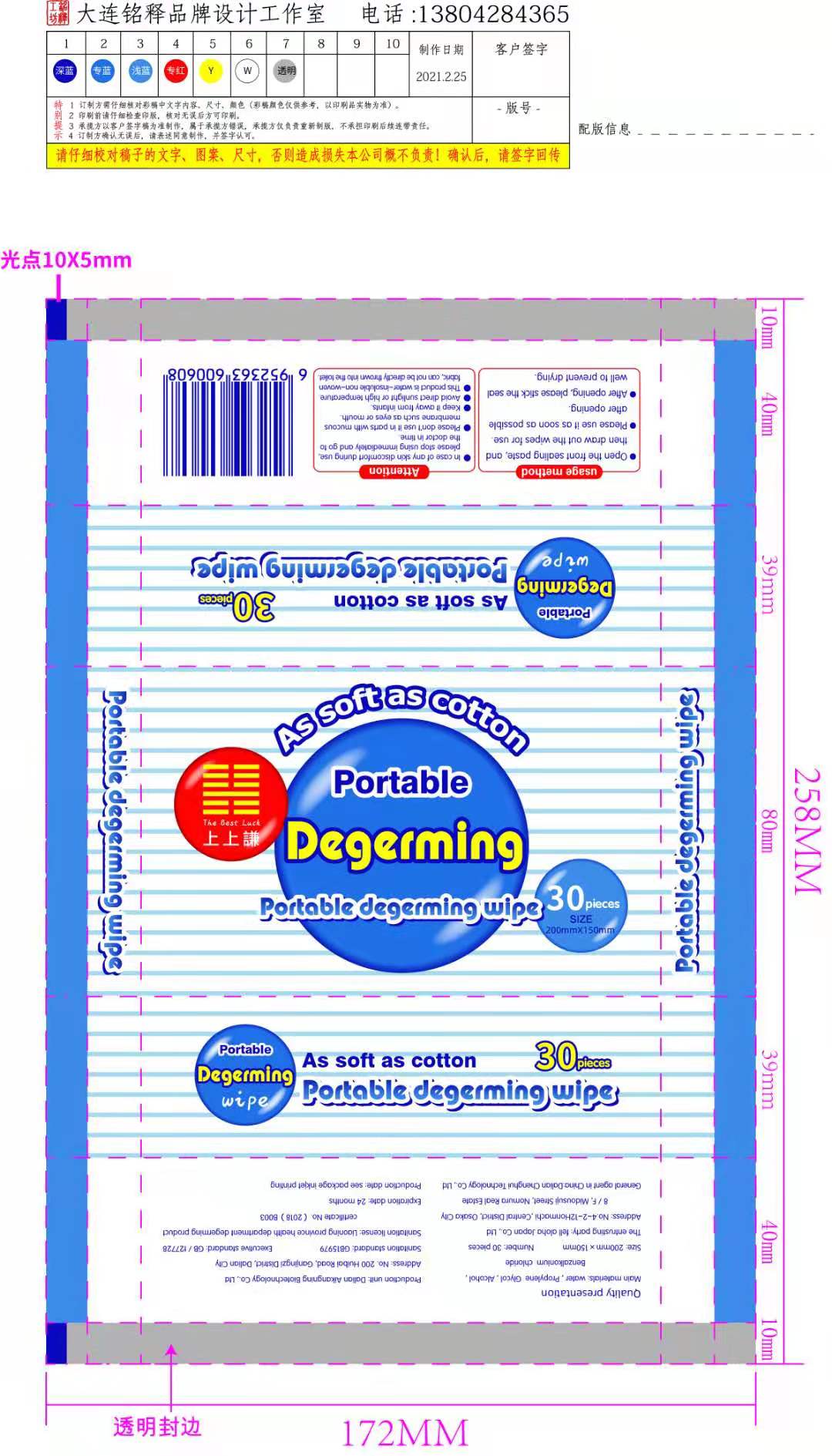 DRUG LABEL: portable degerming wipe
NDC: 81613-001 | Form: CLOTH
Manufacturer: Dalian Aikangning Biological Technology Co. LTD
Category: otc | Type: HUMAN OTC DRUG LABEL
Date: 20210227

ACTIVE INGREDIENTS: ALCOHOL 30 mL/100 mL
INACTIVE INGREDIENTS: WATER; BENZALKONIUM CHLORIDE; PROPYLENE GLYCOL

Main materials

Alcohol, Benzalkonium chloride

Size: 200mm x 150mm Number: 30 pieces

Sanitation standard: GB15979

Executive standard: GB/127728
Saniltation license: Liaoning province health department degerming product certificate No. (2018) B003
Expiration date: 24 months

PURPOSE

degerming

usage method

- Open the front sealing paste, and then draw out the wipes for use.
- Please use it as soon as possible affer opening
- After opening, please stick the seal well to prevent drying

Attention

- In case of any skin discomfort during use, please stop using immediately and go to the doctor in time
- Please don't use it in parts with mucous membrane such as eyes or mouth
- Keep it away from infants.
- Avoid direct sunlight or high temperature
- This produdt is water-insoluble non-wovon fabric, can not be directly thrown into the toilet.

DO NOT USE

Please don't use it in parts with mucous membrane such as eyes or mouth

WHEN USING

degerming

STOP USE

In case of any skin discomfort during use, please stop using immediately and go to the doctor in time

Keep it away from infants.

DOSAGE AND ADMINISTRATION

Open the front sealing paste, and then draw out the wipes for use.

STORAGE AND HANDLING

expiration date:24 months

Avoid direct sunlight or high temperature

INACTIVE INGREDIENT

water, Propylene Glycol

PACKAGE LABEL

10 pcs: 81613-001-01

20 pcs: 81613-001-02

30 pcs: 81613-001-03

60 pcs: 81613-001-04

80 pcs: 81613-001-05

100 pcs: 81613-001-06

120 pcs: 81613-001-07